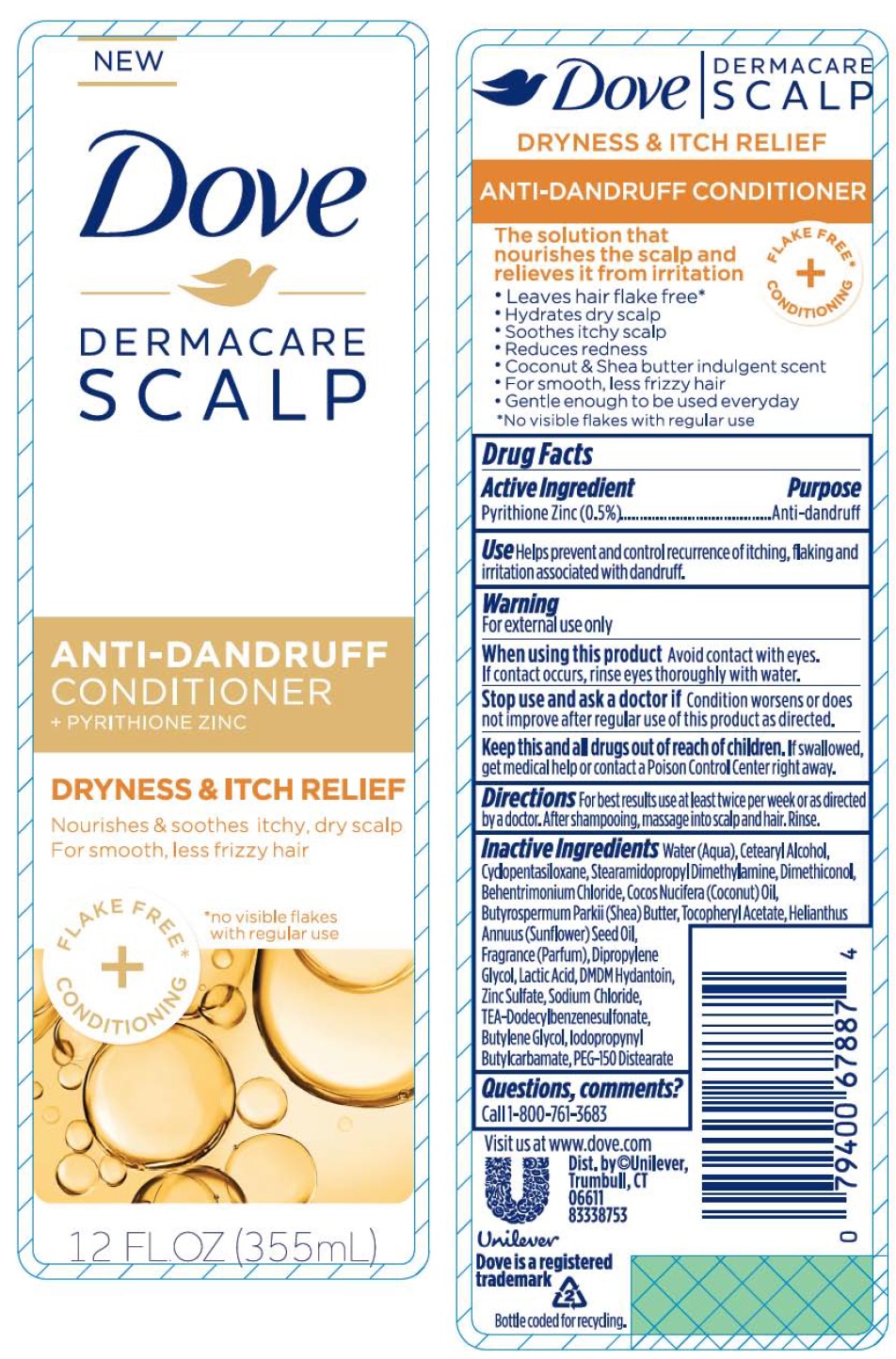 DRUG LABEL: Dove

NDC: 64942-1486 | Form: LIQUID
Manufacturer: Conopco, Inc. d/b/a/ Unilever
Category: otc | Type: HUMAN OTC DRUG LABEL
Date: 20221207

ACTIVE INGREDIENTS: PYRITHIONE ZINC 0.5 g/100 mL
INACTIVE INGREDIENTS: WATER; CETOSTEARYL ALCOHOL; CYCLOMETHICONE 5; STEARAMIDOPROPYL DIMETHYLAMINE; DIMETHICONOL (40 CST); BEHENTRIMONIUM CHLORIDE; COCONUT OIL; SHEA BUTTER; .ALPHA.-TOCOPHEROL ACETATE, D-; SUNFLOWER OIL; DIPROPYLENE GLYCOL; LACTIC ACID, UNSPECIFIED FORM; DMDM HYDANTOIN; ZINC SULFATE, UNSPECIFIED FORM; SODIUM CHLORIDE; TRIETHANOLAMINE DODECYLBENZENESULFONATE; BUTYLENE GLYCOL; IODOPROPYNYL BUTYLCARBAMATE; PEG-150 DISTEARATE

Dove Dermacare Scalp Dryness and Itch Relief Anti-Dandruff Conditioner

Active Ingredient

Pyrithione Zinc (0.5%)

Purpose

Anti-dandruff

Use

Helps prevent and control recurrence of itching, flaking and irritation associated with dandruff.

Warning

For external use only
When using this product Avoid contact with eyes. If contact occurs, rinse eyes thoroughly with water.
Stop use and ask a doctor if Condition worsens or does not improve after regular use of this product as directed.

KEEP OUT OF REACH OF CHILDREN

Keep this and all drugs out of reach of children. If swallowed, get medical help or contact a Poison Control Center right away.

Directions

For best results use at least twice per week or as directed by a doctor. After shampooing, massage into scalp and hair. Rinse.

Inactive Ingredients

Water(Aqua), Cetearyl Alcohol, Cyclopentasiloxne, Stearamidopropyl Dimethylamine, Dimethiconol, Behentrimonium Chloride, Cocos Nucifera(Coconut)Oil, Butyrospermum Parkii(Shea)Butter, Tocopheryl Acetate, Helianthus Annuus(Sunflower)Seed Oil, Fragrance(Parfum), Dipropylene Glycol, Lactic Acid, DMDM Hydantoin, Zinc Sulfate, Sodium Chloride, TEA-Dodecylbenzenesulfonate, Butylene Glycol, Iodopropynyl Butylcarbamate, PEG-150 Distearate

Questions, comments?

Call 1-800-761-3683

Nourishes & soothes itchy, dry scalp

For smooth, less frizzy hair
FLAKE FREE* + CONDITIONING
The solution that nourishes the scalp and relieves it from irritation

- Leaves hair flake free*
- Hydrates dry scalp
- Soothes itchy scalp
- Reduces redness
- Coconut & Shea butter indulgent scent
- For smooth, less frizzy hair
- Gentle enough to be used everyday

*No visible flakes with regular use